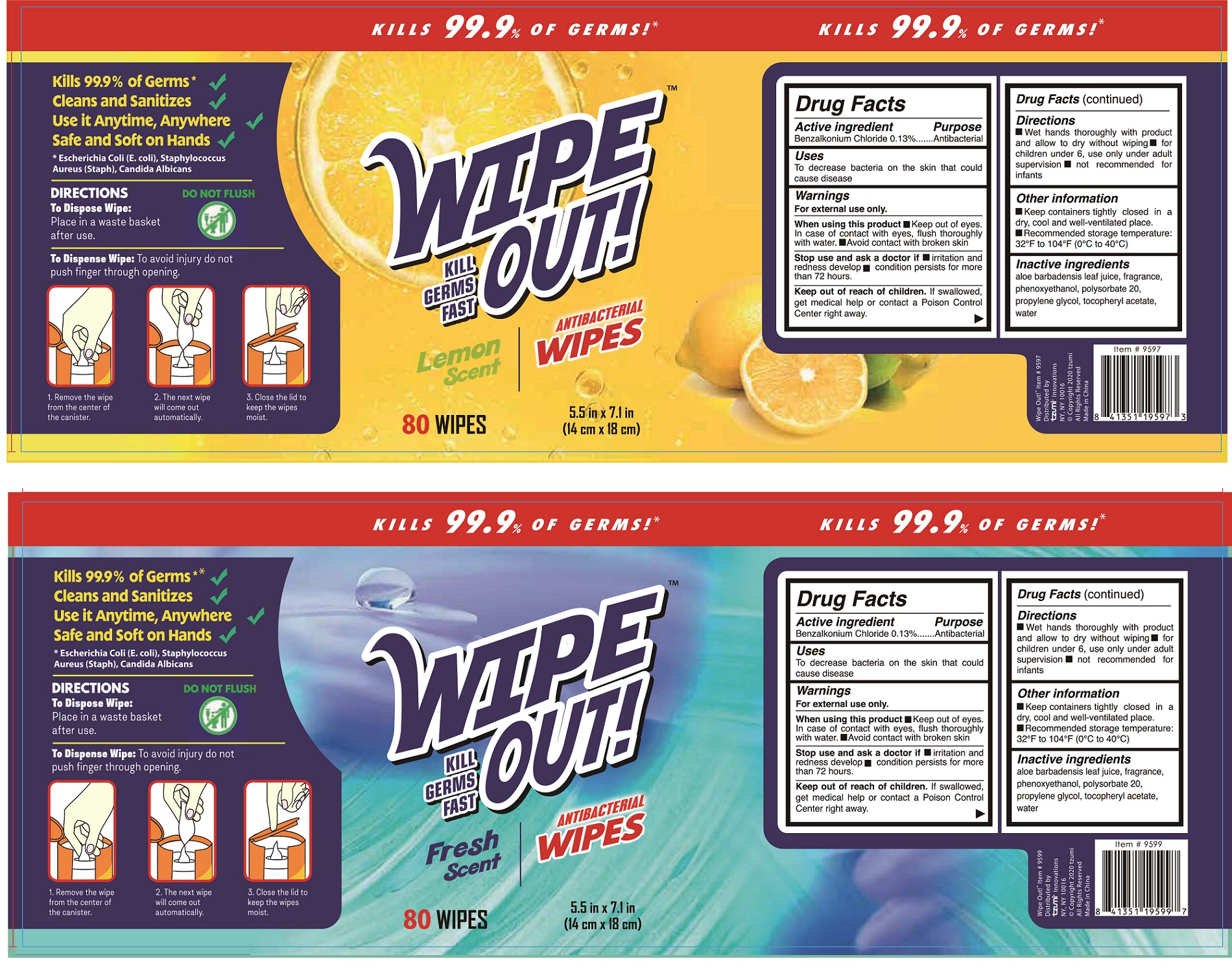 DRUG LABEL: Antibacterial Wipes
NDC: 80153-001 | Form: CLOTH
Manufacturer: Hangzhou Youyi Nonwoven Co., Ltd.
Category: otc | Type: HUMAN OTC DRUG LABEL
Date: 20200819

ACTIVE INGREDIENTS: BENZALKONIUM CHLORIDE 0.13 g/100 g
INACTIVE INGREDIENTS: ALPHA-TOCOPHEROL ACETATE; PHENOXYETHANOL; POLYSORBATE 20; WATER; ALOE VERA LEAF; PROPYLENE GLYCOL

80153-001 Antibacterial wipes 0.13% Benzalkonium Chloride

Active Ingredient(s)

Benzalkonium Chloride 0.13%

Purpose

Antibacterial

Use

To decrease bacteria on the skin that could
cause disease

Warnings

For external use only.
When using this product■Keep out of eyes.
In case of contact with eyes, flush thoroughly
with water. I I Avoid contact with broken skin
Stop use and ask a doctor if■irritation and
redness develop■condition persists for more
than 72 hours.

Keep out of reach of children. If swallowed,
get medical help or contact a Poison Control Center right away.

Directions

Wet hands thoroughly with product
and allow to dry without wiping■for
children under 6, use only under adult
supervision■not recommended for
infants

Inactive ingredients

aloe barbadensis leaf juice, fragrance,
phenoxyethanol, polysorbate 20,
propylene glycol, tocopheryI acetate,
water